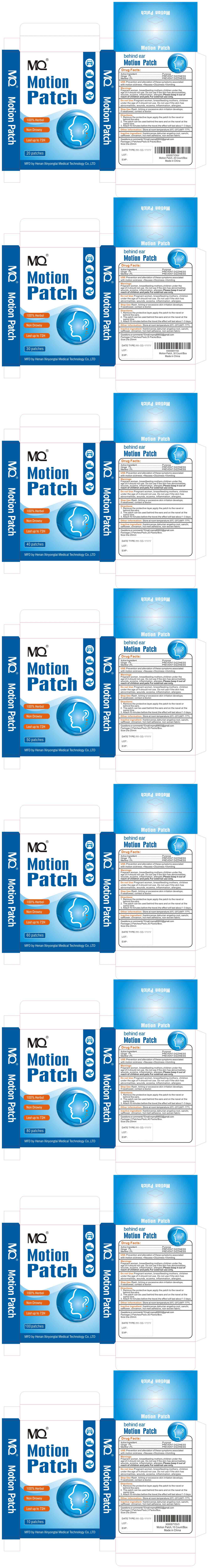 DRUG LABEL: MQ Motion Patch
NDC: 83781-012 | Form: PATCH
Manufacturer: Zhengzhou Miaoqi Medical Technology Co., Ltd.
Category: otc | Type: HUMAN OTC DRUG LABEL
Date: 20250721

ACTIVE INGREDIENTS: MENTHOL 2 g/100 1; GINGER 1 g/100 1
INACTIVE INGREDIENTS: SAFFLOWER; ALYSICARPUS RUGOSUS WHOLE; ANGELICA DAHURICA ROOT; PANAX NOTOGINSENG ROOT; CINNAMON; DIETHYLENE GLYCOL ABIETATE; FRANKINCENSE

83781-012

Active Ingredient

Ginger 1%
Menthol 2%

Purpose

PREVENT DIZZINESS

Use

Prevention and alleviation of these symptoms associated with motion sickness: ·Nausea ·Dizziness ·Vomiting

Warnings

Pregnant women, breastfeeding mothers,children under the age of 4 should not use.Do not use if the skin has abnormalities, wounds, eczema, inflammation, allergies.Please keep it out of reach of children and pets.For external use only.

Do not use

Pregnant women, breastfeeding mothers, children under the age of 4 should not use. Do not use if the skin has abnormalities, wounds, eczema, inflammation, allergies.

Stop Use

rash, itching or excessive skin irritation develops Ifswallowed,contactadoctor.

Ask Doctor

If swallowed, contact a doctor.

Keep Out Of Reach Of Children

Please keep it out of reach of children and pets.
For external use only.

Directions

1.Remove the protective layer, apply the patch to the navel or behind the ears.
2. The patch can be used behind the ears and on the navel at the same time.
3.Attach 10 minutes before the travel, the effect will last about 1-3 days.

Other information

Store at room temperature 20℃-25℃(68℉-77℉)

Inactive ingredients

frankincense, dahurian angelica root，sanchi, safflower，cinnamon, hot melt adhesive,non-woven fabric

Questions

Questions or comments?

Email:mqmq69002@gmail.com